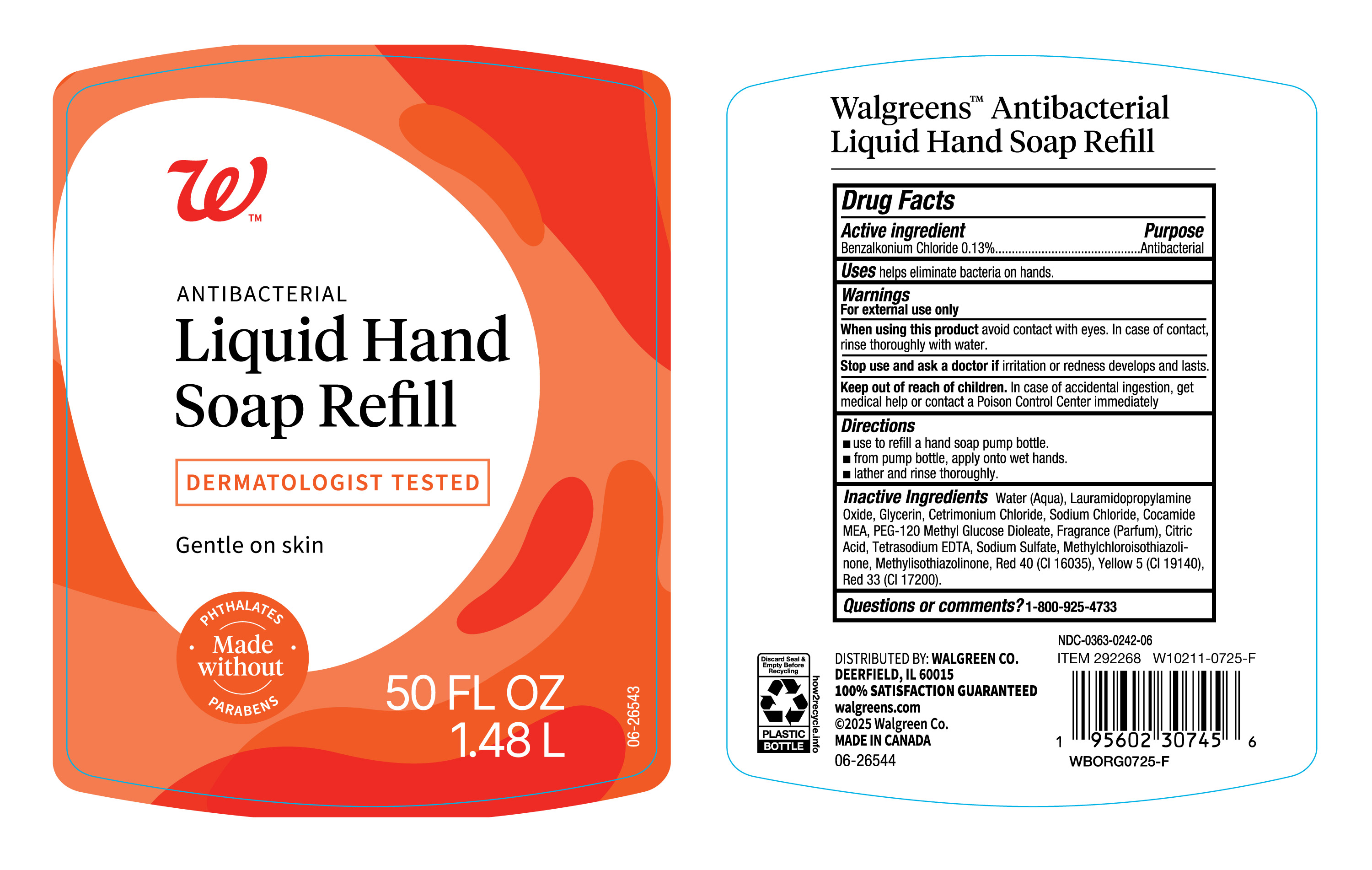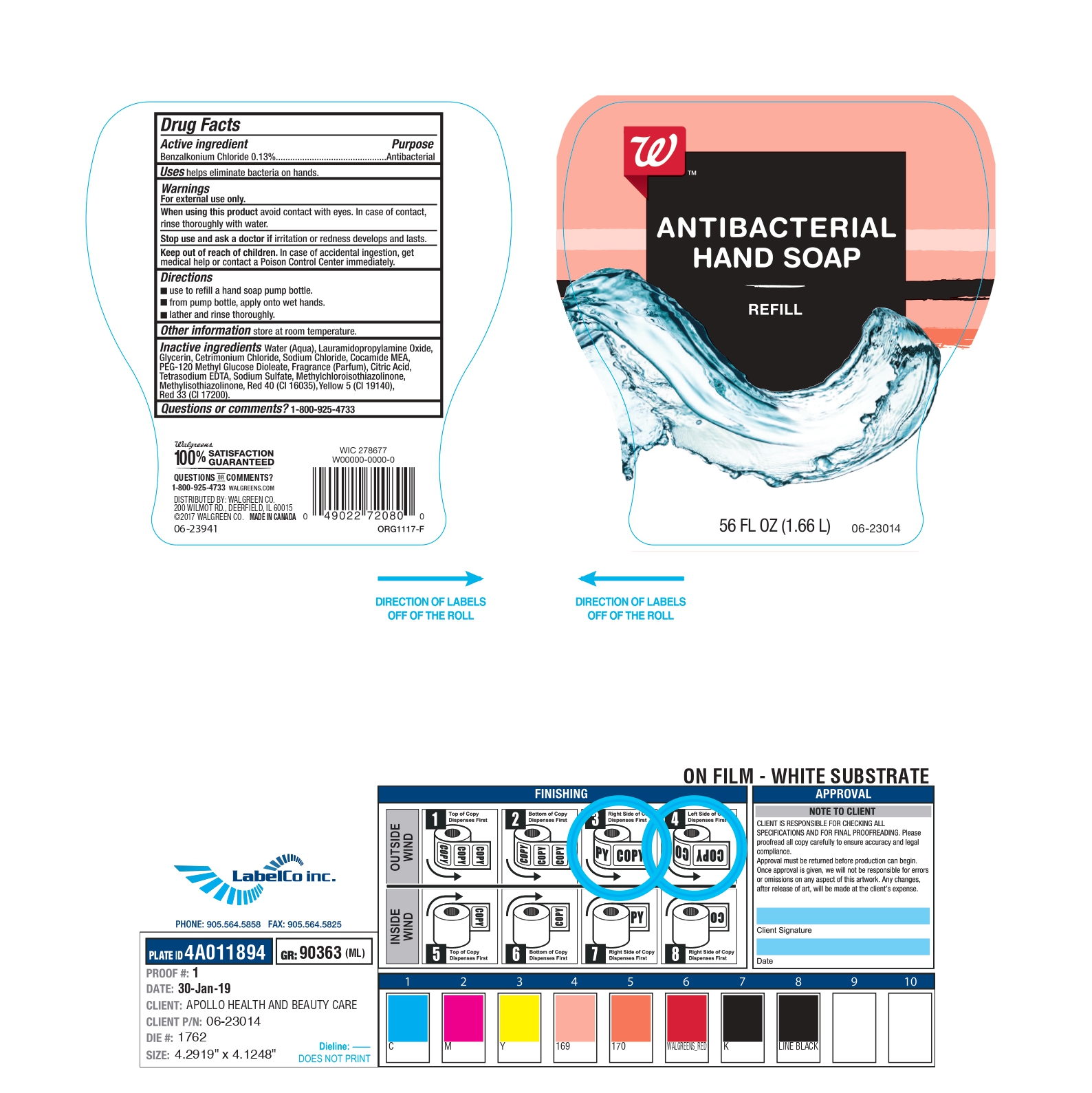 DRUG LABEL: Walgreen
NDC: 0363-0242 | Form: SOAP
Manufacturer: Walgreen Co
Category: otc | Type: HUMAN OTC DRUG LABEL
Date: 20250820

ACTIVE INGREDIENTS: BENZALKONIUM CHLORIDE 130 mg/100 mL
INACTIVE INGREDIENTS: PEG-120 METHYL GLUCOSE DIOLEATE; FRAGRANCE CLEAN ORC0600327; CITRIC ACID MONOHYDRATE; EDETATE SODIUM; SODIUM SULFATE; FD&C YELLOW NO. 5; FD&C RED NO. 40; D&C RED NO. 33; METHYLCHLOROISOTHIAZOLINONE; WATER; LAURAMIDOPROPYLAMINE OXIDE; GLYCERIN; CETRIMONIUM CHLORIDE; SODIUM CHLORIDE; METHYLISOTHIAZOLINONE; COCO MONOETHANOLAMIDE

Walgreens Handsoap-0363-0242

Active Ingredient.

Benzalkonium Chloride (0.13%)

Purpose

Antibacterial

Uses

helps eliminate bacteria on hands.

Warnings

For external use only

When using this product

Avoid contact with eyes. In case of contact, rinse thoroughly with water.

Stop use and ask a doctor if

irritation or redness develops and lasts

Keep out of reach of children.

In case of accidental ingestion, get medical help or contact Poison Control Center immediately.

Directions

- use to refill soap pump bottle
- from pump bottle, apply onto wet hands
- Lather and rinse thoroughly.

Other Information

Store at room temperature

Inactive Ingredients

Water (Aqua), Lauramidopropylamine Oxide, Glycerin, Cetrimonium Chloride, Sodium Chloride, Cocamide MEA, PEG-120 Methyl Glucose Dioleate, Fragrance (Parfum), Citric Acid, Tetrasodium EDTA, Sodium Sulfate, Methylchloroisothiazolinone, Methylisothiazolinone, Red 40 (Cl 16035), Yellow 5 (Cl 19140), Red 33 (Cl 17200).

Questions or comments?

1-800-925-4733